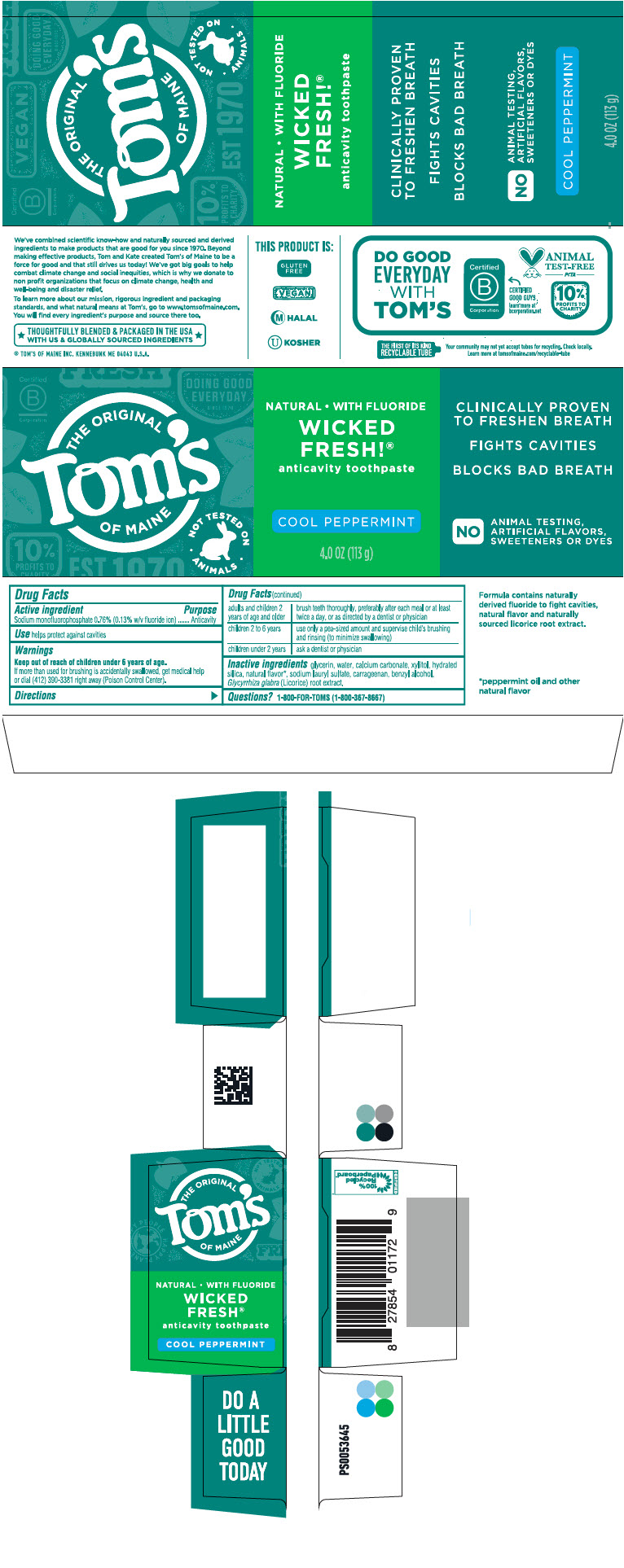 DRUG LABEL: Toms Wicked Fresh Cool Peppermint
NDC: 51009-205 | Form: PASTE, DENTIFRICE
Manufacturer: Tom's of Maine, Inc.
Category: otc | Type: HUMAN OTC DRUG LABEL
Date: 20241024

ACTIVE INGREDIENTS: SODIUM MONOFLUOROPHOSPHATE 1.4 mg/1 g
INACTIVE INGREDIENTS: GLYCERIN; WATER; CALCIUM CARBONATE; XYLITOL; HYDRATED SILICA; SODIUM LAURYL SULFATE; CARRAGEENAN; BENZYL ALCOHOL; LICORICE

Tom's Wicked Fresh® Cool Peppermint Toothpaste
fresh breath / cavity protection

Drug Facts

Active ingredient

Sodium monofluorophosphate 0.76% (0.13% w/v fluoride ion)

Purpose

Anticavity

Use

helps protect against cavities

Warnings

Keep out of reach of children under 6 years of age.

If more than used for brushing is accidentally swallowed, get medical help or dial (412) 390-3381 right away (Poison Control Center).

Directions

adults and children 2 years of age and older | brush teeth thoroughly, preferably after each meal or at least twice a day, or as directed by a dentist or physician
children 2 to 6 years | use only a pea-sized amount and supervise child's brushing and rinsing (to minimize swallowing)
children under 2 years | ask a dentist or physician

Inactive ingredients

glycerin, water, calcium carbonate, xylitol, hydrated silica, natural flavor [peppermint oil and other natural flavor] , sodium lauryl sulfate, carrageenan, benzyl alcohol, Glycyrrhiza glabra (Licorice) root extract.

Questions?

1-800-FOR-TOMS (1-800-367-8667)

PRINCIPAL DISPLAY PANEL - 113 g Tube Carton

THE ORIGINAL
Toms's
OF MAINE

NOT TESTED ON
• ANIMALS •

NATURAL • WITH FLUORIDE

WICKED
FRESH!®

anticavity toothpaste

COOL PEPPERMINT

4.0 OZ (113 g)

CLINICALLY PROVEN
TO FRESHEN BREATH

FIGHTS CAVITIES

BLOCKS BAD BREATH

NO
ANIMAL TESTING,
ARTIFICIAL FLAVORS,
SWEETENERS OR DYES